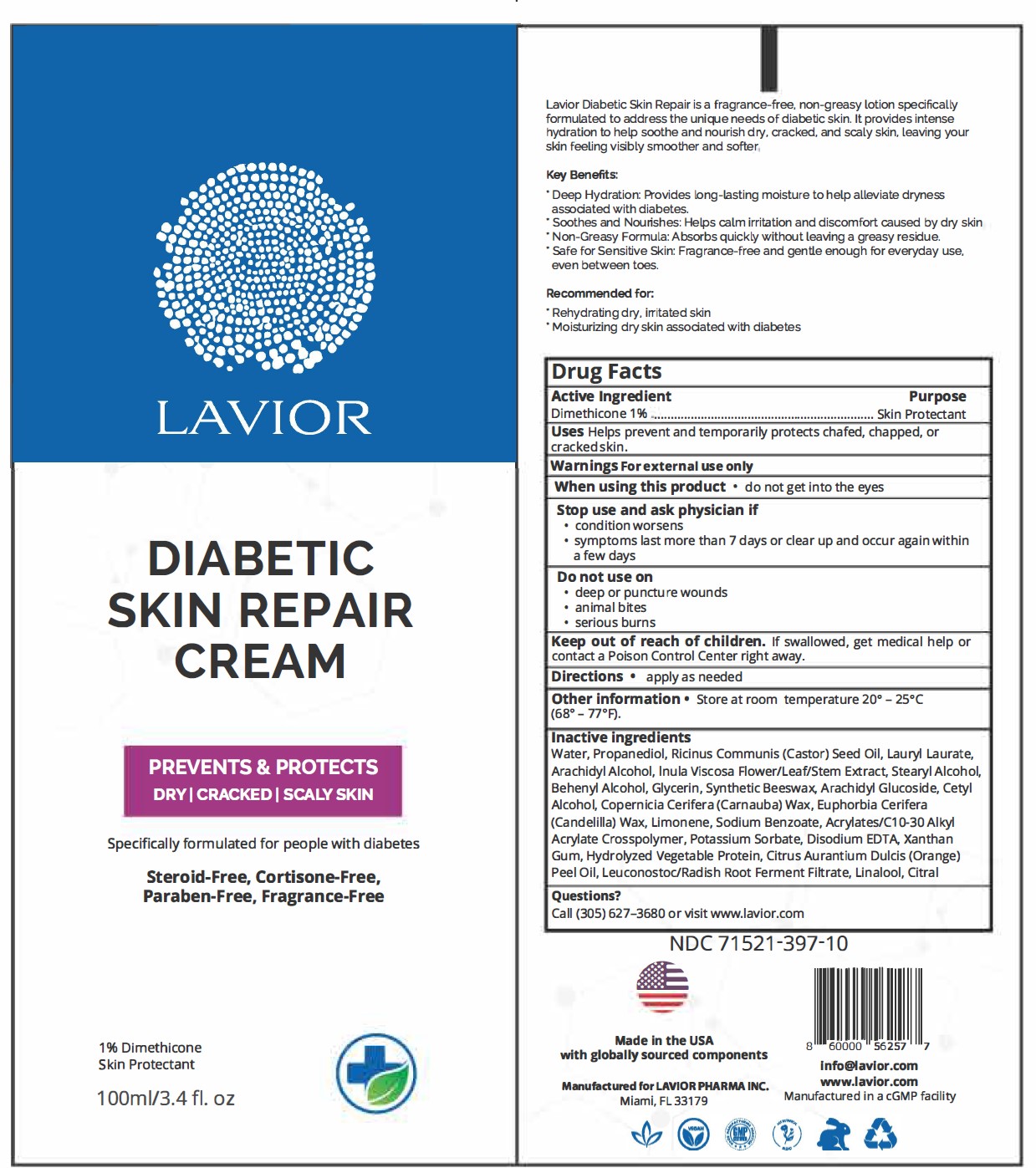 DRUG LABEL: Diabetic Skin Repair Cream
NDC: 71521-397 | Form: CREAM
Manufacturer: Lavior Pharma Inc
Category: otc | Type: HUMAN OTC DRUG LABEL
Date: 20241022

ACTIVE INGREDIENTS: DIMETHICONE 1 g/100 g
INACTIVE INGREDIENTS: POTASSIUM SORBATE; LIMONENE, (+)-; CARBOMER INTERPOLYMER TYPE A (55000 CPS); XANTHAN GUM; CARNAUBA WAX; EDETATE DISODIUM; STEARYL ALCOHOL; CETYL ALCOHOL; LAURYL LAURATE; ARACHIDYL ALCOHOL; SYNTHETIC BEESWAX; CASTOR OIL; CITRAL; ARACHIDYL GLUCOSIDE; PROPANEDIOL; SODIUM BENZOATE; LEUCONOSTOC/RADISH ROOT FERMENT FILTRATE; GLYCERIN; DOCOSANOL; LINALOOL; DITTRICHIA VISCOSA WHOLE; CANDELILLA WAX; ORANGE OIL

Active Ingredient

Dimethicone 1%..............................Skin Protectant

Purpose

Skin Protectant

Uses

Helps prevent and temporarily protects chafed, chapped, or cracked skin.

Warnings

For external use only

When using this product

Do not get into the eyes

Stop use and ask a physician if

- condition worsens
- symptoms last more than 7 days or clear up and occur again within a few days

Do not use on

- deep or puncture wounds
- animal bites
- serious burns

Keep out of reach of children

If swallowed, get medical help or contact a Poison Control Center right away.

Directions

Apply as needed.

Other information

Store at 20° – 25°C (68° – 77°F).

Inactive Ingredients

Water, Propanediol, Ricinus Communis (Castor) Seed Oil, Lauryl Laurate, Arachidyl Alcohol, Inula Viscosa Flower/Leaf/Stem Extract, Stearyl Alcohol, Behenyl Alcohol, Glycerin, Synthetic Beeswax, Arachidyl Glucoside, Cetyl Alcohol, Copernicia Cerifera (Carnauba) Wax, Euphorbia Cerifera (Candelilla) Wax, Limonene, Sodium Benzoate, Acrylates/C10-30 Alkyl Acrylate Crosspolymer, Potassium Sorbate, Disodium EDTA, Xanthan Gum, Hydrolyzed Vegetable Protein, Citrus Aurantium Dulcis (Orange) Peel Oil, Leuconostoc/Radish Root Ferment Filtrate, Linalool, Citral

Questions?

Call (305) 627-3680 or visit www.lavior.com